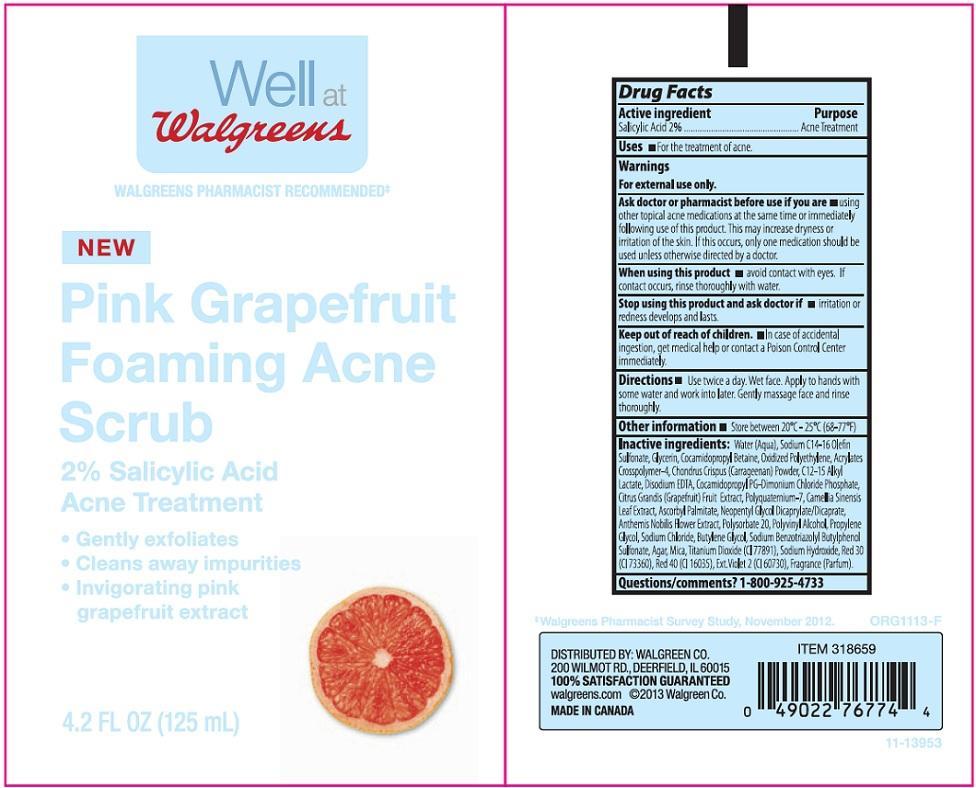 DRUG LABEL: WALGREENS
NDC: 0363-0828 | Form: LIQUID
Manufacturer: WALGREEN COMPANY
Category: otc | Type: HUMAN OTC DRUG LABEL
Date: 20131218

ACTIVE INGREDIENTS: SALICYLIC ACID 20 mg/1 mL
INACTIVE INGREDIENTS: WATER; SODIUM C14-16 OLEFIN SULFONATE; GLYCERIN; COCAMIDOPROPYL BETAINE; HIGH DENSITY POLYETHYLENE; CARBOMER COPOLYMER TYPE A (ALLYL PENTAERYTHRITOL CROSSLINKED); CHONDRUS CRISPUS; C12-15 ALKYL LACTATE; EDETATE DISODIUM; COCAMIDOPROPYL PG-DIMONIUM CHLORIDE PHOSPHATE; PUMMELO; POLYQUATERNIUM-7 (70/30 ACRYLAMIDE/DADMAC; 1600000 MW); GREEN TEA LEAF; ASCORBYL PALMITATE; NEOPENTYL GLYCOL DICAPRYLATE/DICAPRATE; CHAMAEMELUM NOBILE FLOWER; POLYSORBATE 20; POLYVINYL ALCOHOL; PROPYLENE GLYCOL; SODIUM CHLORIDE; BUTYLENE GLYCOL; SODIUM BENZOTRIAZOLYL BUTYLPHENOL SULFONATE; AGAR; MICA; TITANIUM DIOXIDE; SODIUM HYDROXIDE; D&C RED NO. 30; FD&C RED NO. 40; EXT. D&C VIOLET NO. 2

DRUG FACTS

ACTIVE INGREDIENT

SALICYLIC ACID 2%

PURPOSE

ACNE TREATMENT

USES

FOR THE TREATMENT OF ACNE

WARNINGS

FOR EXTERNAL USE ONLY

ASK DOCTOR OR PHARMACIST BEFORE USE IF YOU ARE

USING OTHER TOPICAL ACNE MEDICATIONS AT THE SAME TIME OR IMMEDIATELY FOLLOWING USE OF THIS PRODUCT. THIS MAY INCREASE DRYNESS OR IRRITATION OF THE SKIN. IF THIS OCCURS, ONLY ONE MEDICATION SHOULD BE USED UNLESS OTHERWISE DIRECTED BY A DOCTOR

WHEN USING THIS PRODUCT

AVOID CONTACT WITH EYES. IF CONTACT OCCURS, RINSE THOROUGHLY WITH WATER

STOP USING THIS PRODUCT AND ASK DOCTOR IF

IRRITATION OR REDNESS DEVELOPS AND LASTS

KEEP OUT OF REACH OF CHILDREN

IN CASE OF ACCIDENTAL INGESTION, GET MEDICAL HELP OR CONTACT A POISON CONTROL CENTER IMMEDIATELY

DIRECTIONS

USE TWICE A DAY. WET FACE. APPLY TO HANDS WITH SOME WATER AND WORK INTO LATHER. GENTLY MASSAGE FACE AND RINSE THOROUGHLY

OTHER INFORMATION

STORE BETWEEN 20°C - 25°C (68-77°F)

INACTIVE INGREDIENTS

WATER (AQUA), SODIUM C14-16 OLEFIN SULFONATE, GLYCERIN, COCAMIDOPROPYL BETAINE, OXIDIZED POLYETHYLENE, ACRYLATES CROSSPOLYMER-4, CHONDRUS CRISPUS (CARRAGEENAN) POWDER, C12-15 ALKYL LACTATE, DISODIUM EDTA, COCAMIDOPROPYL PG-DIMONIUM CHLORIDE PHOSPHATE, CITRUS GRANDIS (GRAPEFRUIT) FRUIT EXTRACT, POLYQUATERNIUM-7, CAMELLIA SINENSIS LEAF EXTRACT, ASCORBYL PALMITATE, NEOPENTYL GLYCOL DICAPRYLATE/DICAPRATE, ANTHEMIS NOBILIS FLOWER EXTRACT, POLYSORBATE 20, POLYVINYL ALCOHOL, PROPYLENE GLYCOL, SODIUM CHLORIDE, BUTYLENE GLYCOL, SODIUM BENZOTRIAZOLYL BUTYLPHENOL SULFONATE, AGAR, MICA, TITANIUM DIOXIDE (CI 77891), SODIUM HYDROXIDE, RED 30 (CI 73360), RED 40 (CI 16035), EXT. VIOLET 2 (CI 60730), FRAGRANCE (PARFUM)

QUESTIONS/COMMENTS?

1-800-925-4733